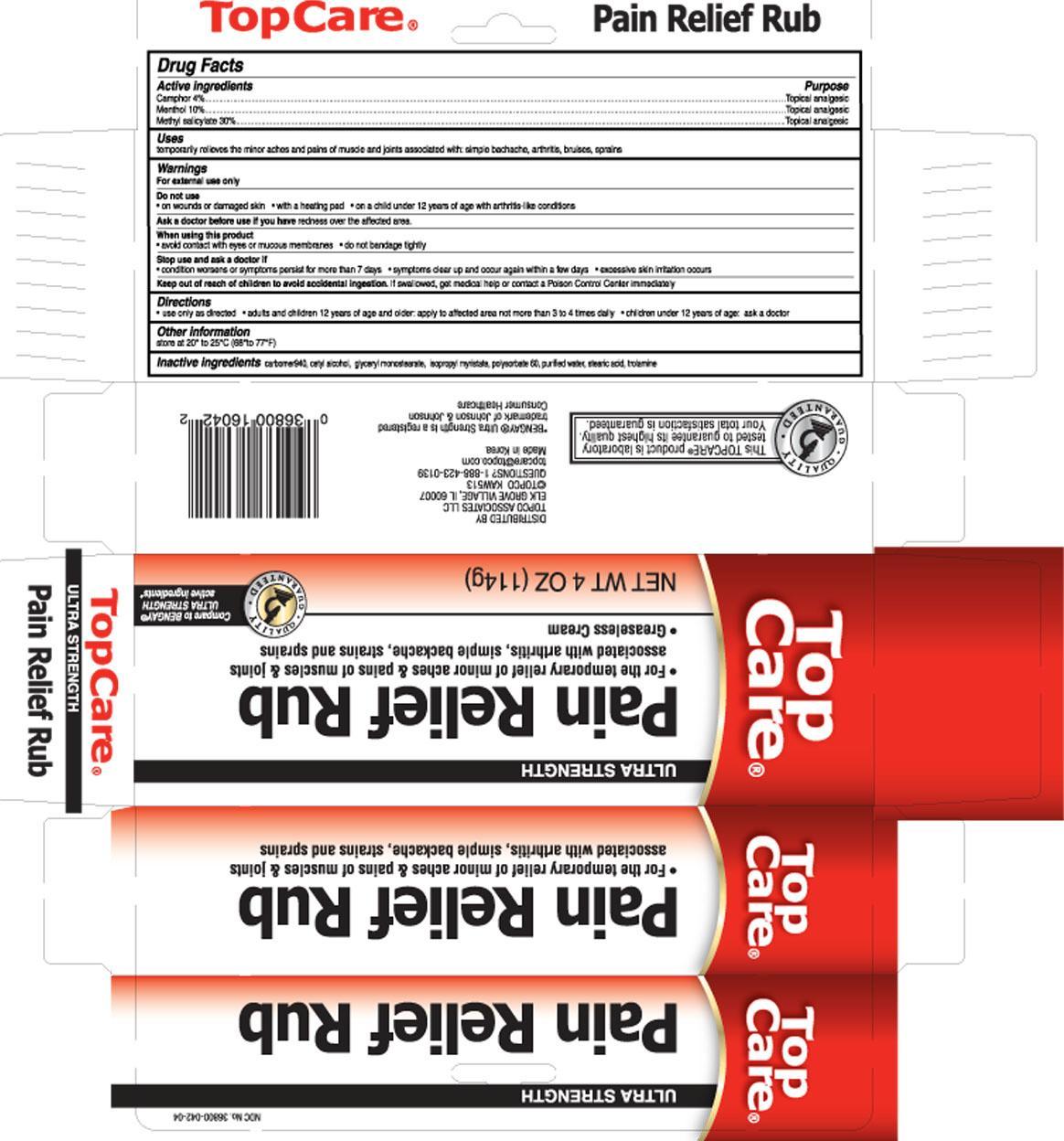 DRUG LABEL: Pain Relief Rub
NDC: 36800-042 | Form: CREAM
Manufacturer: Topco Associates LLC
Category: otc | Type: HUMAN OTC DRUG LABEL
Date: 20130726

ACTIVE INGREDIENTS: MENTHOL 10 g/100 g; MENTHYL SALICYLATE, (+/-)- 30 g/100 g; Camphor (Natural) 4 g/100 g
INACTIVE INGREDIENTS: CARBOMER 940; CETYL ALCOHOL; GLYCERYL MONOSTEARATE; ISOPROPYL MYRISTATE; POLYSORBATE 60; WATER; STEARIC ACID; TROLAMINE

Drug Facts

Active Ingredients

Camphor 4%

Menthol 10%

Methyl Salicylate 30%

Uses

temporarily relieves the minor aches and pains of muscle and joints associated with: simple backache, arthritis, bruises, sprains

WARNINGS

For external use only.

Do not use

- on wounds or damaged skin
- with a heating pad
- on a child under 12 years of age with arthritis-like conditions

Ask a doctor before use if you have

redness over the affected area

When using this product

- avoid contact with eyes or mucous membranes
- do not bandage tightly

Stop use and ask a doctor if

- condition worsens or symptoms persist for more than 7 days
- symptoms clear up and occur again within a few days
- excessive skin irritation occurs

Keep out of reach of children to avoid accidental ingestion.

If swallowed, get medical help or contact a Poison Control Center immediately

Directions

- Use only as directed
- adults and children 12 years of age and older:

apply to affected area not more than 3 to 4 times daily

- children under 12 years of age: ask a doctor

Other information

- Store at 20° to 25°C (68°to 77°F)

Inactive Ingredients

carbomer940, cetyl alcohol, glyceryl monostearate, isopropyl myristate, polysorbate60, purified water, stearic acid, trolamine

PACKAGE LABEL

Pain Relief Rub

PURPOSE

Topical analgesic

Topical analgesic

Topical analgesic